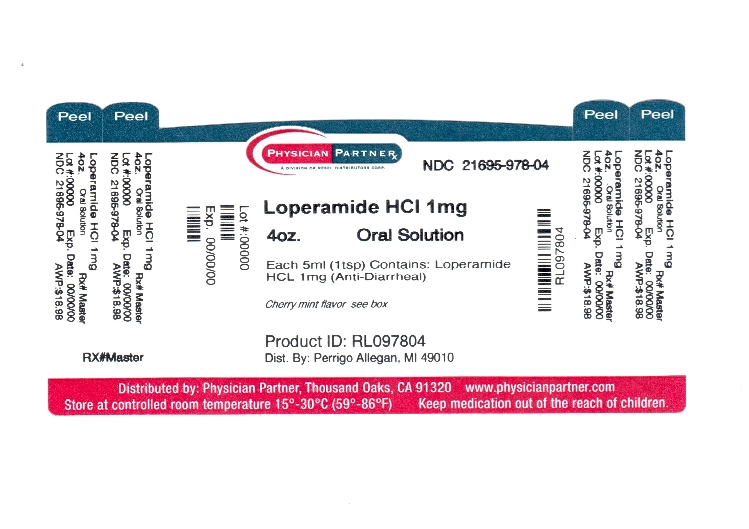 DRUG LABEL: Anti Diarrheal
NDC: 21695-978 | Form: SOLUTION
Manufacturer: Rebel Distributors Corp
Category: otc | Type: HUMAN OTC DRUG LABEL
Date: 20110913

ACTIVE INGREDIENTS: LOPERAMIDE HYDROCHLORIDE 1 mg/5 mL
INACTIVE INGREDIENTS: ALCOHOL; BENZOIC ACID; CITRIC ACID MONOHYDRATE; GLYCERIN; PROPYLENE GLYCOL; WATER; SODIUM BENZOATE; SORBITOL; SUCROSE

Rite Aid Corporation Anti-Diarrheal Drug Facts

Active ingredient (in each 5 mL)

Loperamide HCl 1 mg

Purpose

Anti-diarrheal

Uses

controls symptoms of diarrhea, including Travelers’ Diarrhea

Warnings

Allergy alert: Do not use if you have ever had a rash or other allergic reaction to loperamide HCl

Do not use

if you have bloody or black stool

Ask a doctor before use if you have

- fever
- mucus in the stool
- a history of liver disease

Ask a doctor or pharmacist before use if you are

taking antibiotics

When using this product

- tiredness, drowsiness or dizziness may occur. Be careful when driving or operating machinery.

Stop use and ask a doctor if

- symptoms get worse
- diarrhea lasts for more than 2 days
- you get abdominal swelling or bulging. These may be signs of a serious condition.

If pregnant or breast-feeding,

ask a health professional before use.

Keep out of reach of children.

In case of overdose, get medical help or contact a Poison Control Center right away.

Directions

- drink plenty of clear fluids to help prevent dehydration caused by diarrhea
- find right dose on chart. If possible, use weight to dose; otherwise use age.
- only use attached measuring cup to dose product

adults and children 12 years and over | 4 teaspoonfuls (1 dosage cup) after the first loose stool; 2 teaspoonfuls (1/2 dosage cup) after each subsequent loose stool; but no more than 8 teaspoonfuls in 24 hours
children 9-11 years (60-95 lbs) | 2 teaspoonfuls (1/2 dosage cup) after the first loose stool; 1 teaspoonful (1/4 dosage cup) after each subsequent loose stool; but no more than 6 teaspoonfuls in 24 hours
children 6-8 years (48-59 lbs) | 2 teaspoonfuls (1/2 dosage cup) after the first loose stool; 1 teaspoonful (1/4 dosage cup) after each subsequent loose stool; but no more than 4 teaspoonfuls in 24 hours
children under 6 years (up to 47 lbs) | ask a doctor

Other information

- do not use if carton is opened or if printed plastic neckband is broken or missing
- store between 20°-25°C (68°-77°F)
- see bottom panel for lot number and expiration date

Inactive ingredients

alcohol (0.5%), benzoic acid, citric acid, flavor, glycerin, propylene glycol, purified water, sodium benzoate, sorbitol, sucrose

Questions or comments?

1-800-719-9260